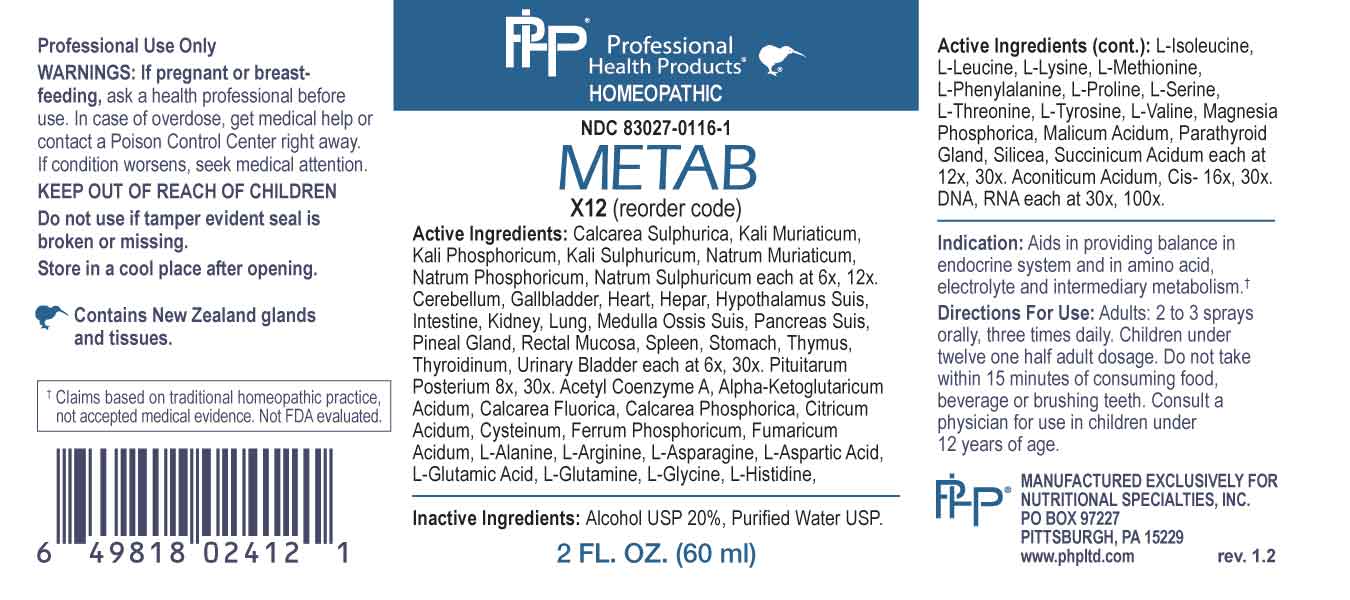 DRUG LABEL: Metab
NDC: 83027-0116 | Form: SPRAY
Manufacturer: Nutritional Specialties, Inc.
Category: homeopathic | Type: HUMAN OTC DRUG LABEL
Date: 20231009

ACTIVE INGREDIENTS: CALCIUM SULFATE ANHYDROUS 6 [hp_X]/1 mL; POTASSIUM CHLORIDE 6 [hp_X]/1 mL; DIBASIC POTASSIUM PHOSPHATE 6 [hp_Q]/1 mL; POTASSIUM SULFATE 6 [hp_X]/1 mL; SODIUM CHLORIDE 6 [hp_X]/1 mL; SODIUM PHOSPHATE, DIBASIC, HEPTAHYDRATE 6 [hp_X]/1 mL; SODIUM SULFATE 6 [hp_X]/1 mL; SUS SCROFA CEREBELLUM 6 [hp_X]/1 mL; BOS TAURUS GALLBLADDER 6 [hp_X]/1 mL; BEEF HEART 6 [hp_X]/1 mL; BEEF LIVER 6 [hp_X]/1 mL; SUS SCROFA HYPOTHALAMUS 6 [hp_X]/1 mL; PORK INTESTINE 6 [hp_X]/1 mL; BEEF KIDNEY 6 [hp_X]/1 mL; BEEF LUNG 6 [hp_X]/1 mL; SUS SCROFA BONE MARROW 6 [hp_X]/1 mL; SUS SCROFA PANCREAS 6 [hp_X]/1 mL; SUS SCROFA PINEAL GLAND 6 [hp_X]/1 mL; SUS SCROFA RECTAL MUCOSA 6 [hp_X]/1 mL; BOS TAURUS SPLEEN 6 [hp_X]/1 mL; SUS SCROFA STOMACH 6 [hp_X]/1 mL; LAMB 6 [hp_X]/1 mL; THYROID, BOVINE 6 [hp_X]/1 mL; SUS SCROFA URINARY BLADDER 6 [hp_X]/1 mL; BOS TAURUS PITUITARY GLAND, POSTERIOR 8 [hp_X]/1 mL; ACETYL COENZYME A 12 [hp_X]/1 mL; OXOGLURIC ACID 12 [hp_X]/1 mL; CALCIUM FLUORIDE 12 [hp_X]/1 mL; TRIBASIC CALCIUM PHOSPHATE 12 [hp_X]/1 mL; ANHYDROUS CITRIC ACID 12 [hp_X]/1 mL; CYSTEINE 12 [hp_X]/1 mL; FERROSOFERRIC PHOSPHATE 12 [hp_X]/1 mL; FUMARIC ACID 12 [hp_X]/1 mL; ALANINE 12 [hp_X]/1 mL; ARGININE 12 [hp_X]/1 mL; ASPARAGINE 12 [hp_X]/1 mL; ASPARTIC ACID 12 [hp_X]/1 mL; GLUTAMIC ACID 12 [hp_X]/1 mL; GLUTAMINE 12 [hp_X]/1 mL; GLYCINE 12 [hp_X]/1 mL; HISTIDINE 12 [hp_X]/1 mL; ISOLEUCINE 12 [hp_X]/1 mL; LEUCINE 12 [hp_X]/1 mL; LYSINE 12 [hp_X]/1 mL; METHIONINE 12 [hp_X]/1 mL; PHENYLALANINE 12 [hp_X]/1 mL; PROLINE 12 [hp_X]/1 mL; SERINE 12 [hp_X]/1 mL; THREONINE 12 [hp_X]/1 mL; TYROSINE 12 [hp_X]/1 mL; VALINE 12 [hp_X]/1 mL; MAGNESIUM PHOSPHATE, DIBASIC TRIHYDRATE 12 [hp_X]/1 mL; MALIC ACID 12 [hp_X]/1 mL; BOS TAURUS PARATHYROID GLAND 12 [hp_X]/1 mL; SILICON DIOXIDE 12 [hp_X]/1 mL; SUCCINIC ACID 12 [hp_X]/1 mL; ACONITIC ACID 16 [hp_X]/1 mL; HERRING SPERM DNA 30 [hp_X]/1 mL; SACCHAROMYCES CEREVISIAE RNA 30 [hp_X]/1 mL
INACTIVE INGREDIENTS: WATER; ALCOHOL

DRUG FACTS:

ACTIVE INGREDIENTS:

Calcarea Sulphurica 6X, 12X, Kali Muriaticum 6X, 12X, Kali Phosphoricum 6X, 12X, Kali Sulphuricum 6X, 12X, Natrum Muriaticum 6X, 12X, Natrum Phosphoricum 6X, 12X, Natrum Sulphuricum 6X, 12X, Cerebellum 6X, 30X, Gallbladder 6X, 30X, Heart 6X, 30X, Hepar 6X, 30X, Hypothalamus Suis 6X, 30X, Intestine 6X, 30X, Kidney 6X, 30X, Lung 6X, 30X, Medulla Ossis Suis 6X, 30X, Pancreas Suis 6X, 30X, Pineal Gland 6X, 30X, Rectal Mucosa 6X, 30X, Spleen 6X, 30X, Stomach6X, 30X, Thymus 6X, 30X, Thyroidinum 6X, 30X, Urinary Bladder 6X, 30X, Pituitarum Posterium 8X, 30X, Acetyl Coenzyme A 12X, 30X, Alpha-Ketoglutaricum Acidum 12X, 30X, Calcarea Fluorica 12X, 30X, Calcarea Phosphorica 12X, 30X, Citricum Acidum 12X, 30X, Cysteinum 12X, 30X, Ferrum Phosphoricum 12X, 30X, Fumaricum Acidum 12X, 30X, L-Alanine 12X, 30X, L-Arginine 12X, 30X, L-Asparagine 12X, 30X, L-Aspartic Acid 12X, 30X, L-Glutamic Acid 12X, 30X, L-Glutamine 12X, 30X, L-Glycine 12X, 30X, L-Histidine 12X, 30X, L-Isoleucine 12X, 30X, L-Leucine 12X, 30X, L-Lysine 12X, 30X, L-Methionine 12X, 30X, L-Phenylalanine 12X, 30X, L-Proline 12X, 30X, L-Serine 12X, 30X, L-Threonine 12X, 30X, L-Tyrosine 12X, 30X, L-Valine 12X, 30X, Magnesia Phosphorica 12X, 30X, Malicum Acidum 12X, 30X, Parathyroid Gland 12X, 30X, Silicea 12X, 30X, Succinicum Acidum 12X, 30X, Aconiticum Acidum Cis 16X, 30X, DNA 30X, 100X, RNA 30X, 100X.

PURPOSE:

Aids in providing balance in endocrine system and in amino acid, electrolyte and intermediary metabolism.†

†Claims based on traditional homeopathic practice, not accepted medical evidence. Not FDA evaluated.

WARNINGS:

Professional Use Only

If pregnant or breast-feeding, ask a health professional before use.

In case of overdose, get medical help or contact a Poison Control Center right away.

If condition worsens, seek medical attention.

KEEP OUT OF REACH OF CHILDREN

Do not use if tamper evident seal is broken or missing.

Store in a cool place after opening

KEEP OUT OF REACH OF CHILDREN:

In case of overdose, get medical help or contact a Poison Control Center right away.

DIRECTIONS:

Adults: 2 to 3 sprays orally, three times daily. Children under twelve one half adult dosage. Do not take within 15 minutes of consuming food, beverage or brushing teeth. Consult a physician for use in children under 12 years of age.

INDICATIONS:

Aids in providing balance in endocrine system and in amino acid, electrolyte and intermediary metabolism.†

†Claims based on traditional homeopathic practice, not accepted medical evidence. Not FDA evaluated.

INACTIVE INGREDIENTS:

Alcohol USP 20%, Purified Water USP.

QUESTIONS:

MANUFACTURED EXCLUSIVELY FOR

NUTRITIONAL SPECIALTIES, INC.

PO BOX 97227

PITTSBURG, PA 15229

www.phpltd.com

PACKAGE LABEL DISPLAY:

Professional

Health Products

HOMEOPATHIC

NDC 83027-0116-1

METAB

2 FL. OZ (60 ml)